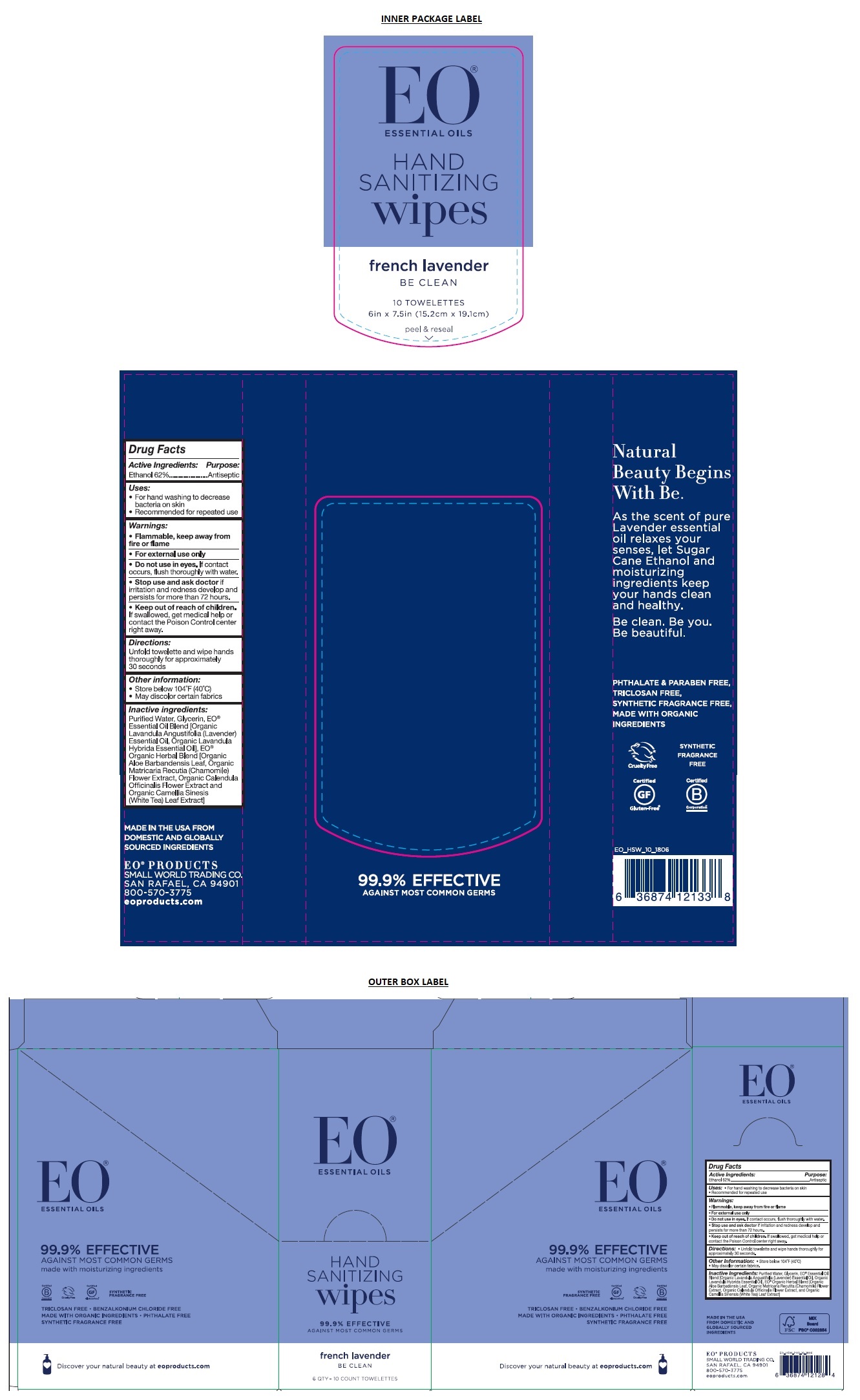 DRUG LABEL: EO Hand Sanitizer Wipes Lavender
NDC: 54748-502 | Form: CLOTH
Manufacturer: EO Products, LLC
Category: otc | Type: HUMAN OTC DRUG LABEL
Date: 20251209

ACTIVE INGREDIENTS: ALCOHOL 62 mL/100 mL
INACTIVE INGREDIENTS: WATER; GLYCERIN; LAVENDER OIL; LAVANDIN OIL; ALOE VERA LEAF; CHAMOMILE; CALENDULA OFFICINALIS FLOWER; GREEN TEA LEAF

EO® Hand Sanitizer Wipes Lavender

Active Ingredients:

Ethanol 62%

Purpose:

Antiseptic

Uses:

- For hand washing to decrease bacteria on skin
- Recommended for repeated use

Warnings:

- Flammable, keep away from fire or flame
- For external use only
- Do not use in eyes. If contact occurs, flush thoroughly with water.
- Stop use and ask a doctor if irritation and redness develop and persists for more than 72 hours.

- Keep out of reach of children. If swallowed, get medical help or contact the Poison Control center right away.

Directions:

- Unfold towelette and wipe hands thoroughly for approximately 30 seconds.

Inactive Ingredients:

Purified Water, Glycerin, EO® Essential Oil Blend [Organic Lavandula Angustifolia (Lavender) Essential Oil, Organic Lavandula Hybrida Essential Oil], EO®Organic Herbal Blend [Organic Aloe Barbadensis Leaf, Organic Matricaria Recutita (Chamomile) Flower Extract, Organic Calendula Officinalis Flower Extract, and Organic Camellia Sinensis(White Tea) Leaf Extract]

Other Information:

- Store below 104°F (40°C)
- May discolor certain fabrics

99.9 % EFFECTIVE AGAINST MOST COMMON GERMS

french lavender

made with moisturizing ingredients

- PHTHALATE & PARABEN FREE
- TRICLOSAN FREE
- BENZALKONIUM CHLORIDE FREE
- MADE WITH ORGANIC INGREDIENTS
- SYNTHETIC FRAGRANCE FREE

Natural Beauty Begins With Be.

As the scent of pure Lavender essential oil relaxes your senses, let Sugar Cane Ethanol and moisturizing ingredients keep your hands clean and healthy.

Be clean. Be you. Be beautiful.

MADE IN THE USA FROM DOMESTIC AND GLOBALLY SOURCED INGREDIENTS

EO® PRODUCTS

SMALL WORLD TRADING CO.

SAN RAFAEL, CA 94901

800-570-3775

eoproducts.com